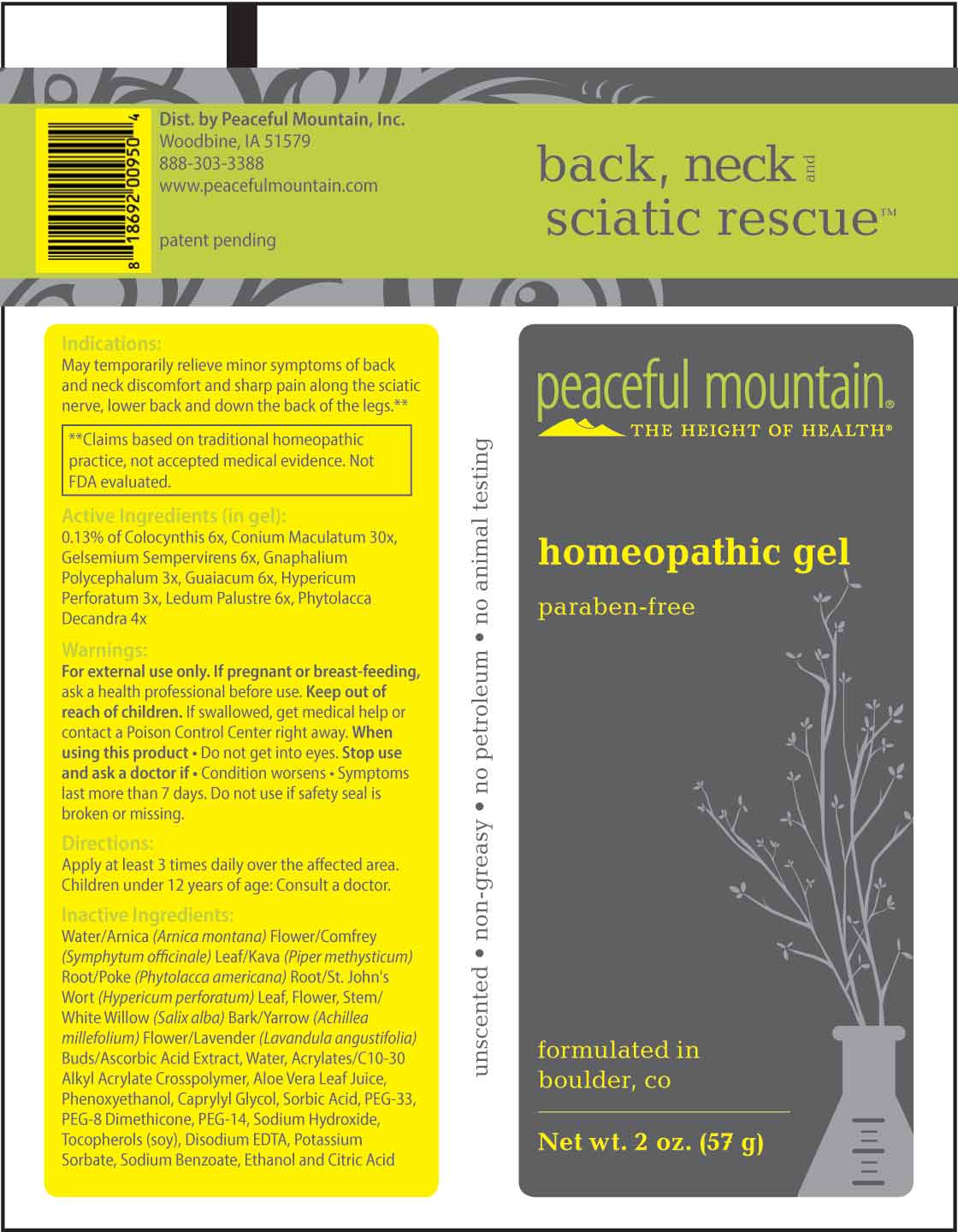 DRUG LABEL: Back, Neck and Sciatic Rescue
NDC: 43846-0076 | Form: GEL
Manufacturer: Peaceful Mountain, Inc.
Category: homeopathic | Type: HUMAN OTC DRUG LABEL
Date: 20250313

ACTIVE INGREDIENTS: PHYTOLACCA AMERICANA ROOT 4 [hp_X]/1 g; PSEUDOGNAPHALIUM OBTUSIFOLIUM WHOLE 3 [hp_X]/1 g; HYPERICUM PERFORATUM WHOLE 3 [hp_X]/1 g; CITRULLUS COLOCYNTHIS FRUIT PULP 6 [hp_X]/1 g; GELSEMIUM SEMPERVIRENS ROOT 6 [hp_X]/1 g; GUAIACUM OFFICINALE RESIN 6 [hp_X]/1 g; RHODODENDRON TOMENTOSUM LEAFY TWIG 6 [hp_X]/1 g; CONIUM MACULATUM FLOWERING TOP 30 [hp_X]/1 g
INACTIVE INGREDIENTS: WATER; PHENOXYETHANOL; CAPRYLYL GLYCOL; SORBIC ACID; SODIUM HYDROXIDE; CARBOMER INTERPOLYMER TYPE A (ALLYL SUCROSE CROSSLINKED); POLYETHYLENE GLYCOL 1600; PEG-8 DIMETHICONE; POLYETHYLENE GLYCOL 700; ALOE VERA LEAF; .ALPHA.-TOCOPHEROL; EDETATE DISODIUM; OREGANO; POTASSIUM SORBATE; ARNICA MONTANA FLOWER; COMFREY LEAF; MACROPIPER METHYSTICUM ROOT; HYPERICUM PERFORATUM FLOWER; SALIX ALBA BARK; ACHILLEA MILLEFOLIUM FLOWER; LAVANDULA ANGUSTIFOLIA SUBSP. ANGUSTIFOLIA FLOWER; ASCORBIC ACID

DRUG FACTS:

ACTIVE INGREDIENTS:

0.13% of Colocynthis 6X, Conium Maculatum 30X, Gelsemium Sempervirens 6X, Gnaphalium Polycephalum 3X, Guaiacum 6X, Hypericum Perforatum 3X, Ledum Palustre 6X, Phytolacca Decandra 4X.

PURPOSE:

May temporarily relieve minor symptoms of back and neck discomfort and sharp pain along the sciatic nerve, lower back and down the back of the legs.**

**Claims based on traditional homeopathic practice, not accepted medical evidence. Not FDA evaluated.

WARNINGS:

For external use only.

If pregnant or breast-feeding, ask a health professional before use.

Keep out of reach of children. If swallowed, get medical help or contact a Poison Control Center right away.

When using this product • Do not get into eyes.

Stop use and ask a doctor if • Conditions worsens · Symptoms last more than 7 days.

Do not use if safety seal is broken or missing.

KEEP OUT OF REACH OF CHILDREN:

If swallowed, get medical help or contact a Poison Control Center right away.

DIRECTIONS:

Apply at least 3 times daily over the affected area.

Children under 12 years of age: Consult a doctor.

INDICATIONS:

May temporarily relieve minor symptoms of back and neck discomfort and sharp pain along the sciatic nerve, lower back and down the back of the legs.**

**Claims based on traditional homeopathic practice, not accepted medical evidence. Not FDA evaluated.

INACTIVE INGREDIENTS:

Water/Arnica (Arnica montana) Flower/Comfrey (Symphytum officinale) Leaf/Kava (Piper methysticum) Root/Poke (Phytolacca americana) Root/St. John's Wort (Hypericum perforatum) Leaf, flower, stem/White Willow (Salix alba) Bark/Yarrow (Achillea millefolium) Flower/Lavender (Lavandula angustifolia) Buds/Ascorbic Acid Extract, Water, Acrylates/C10-30 Alkyl Acrylate Crosspolymer, Aloe Vera Leaf Juice, Phenoxyethanol, Caprylyl Glycol, Sorbic Acid, PEG-33, PEG-8 Dimethicone, PEG-14, Sodium Hydroxide, Tocopherols (soy), Disodium EDTA, Potassium Sorbate, Sodium Benzoate, Ethanol and Citric Acid.

QUESTIONS:

Dist. by Peaceful Mountain, Inc.

Woodbine, IA 51579

888-303-3388

www.peacefulmountain.com

PACKAGE LABEL DISPLAY:

back, neck and

sciatic rescue

peaceful mountain
THE HEIGHT OF HEALTH

homeopathic gel
paraben-free

Net wt. 2 oz. (57 g)